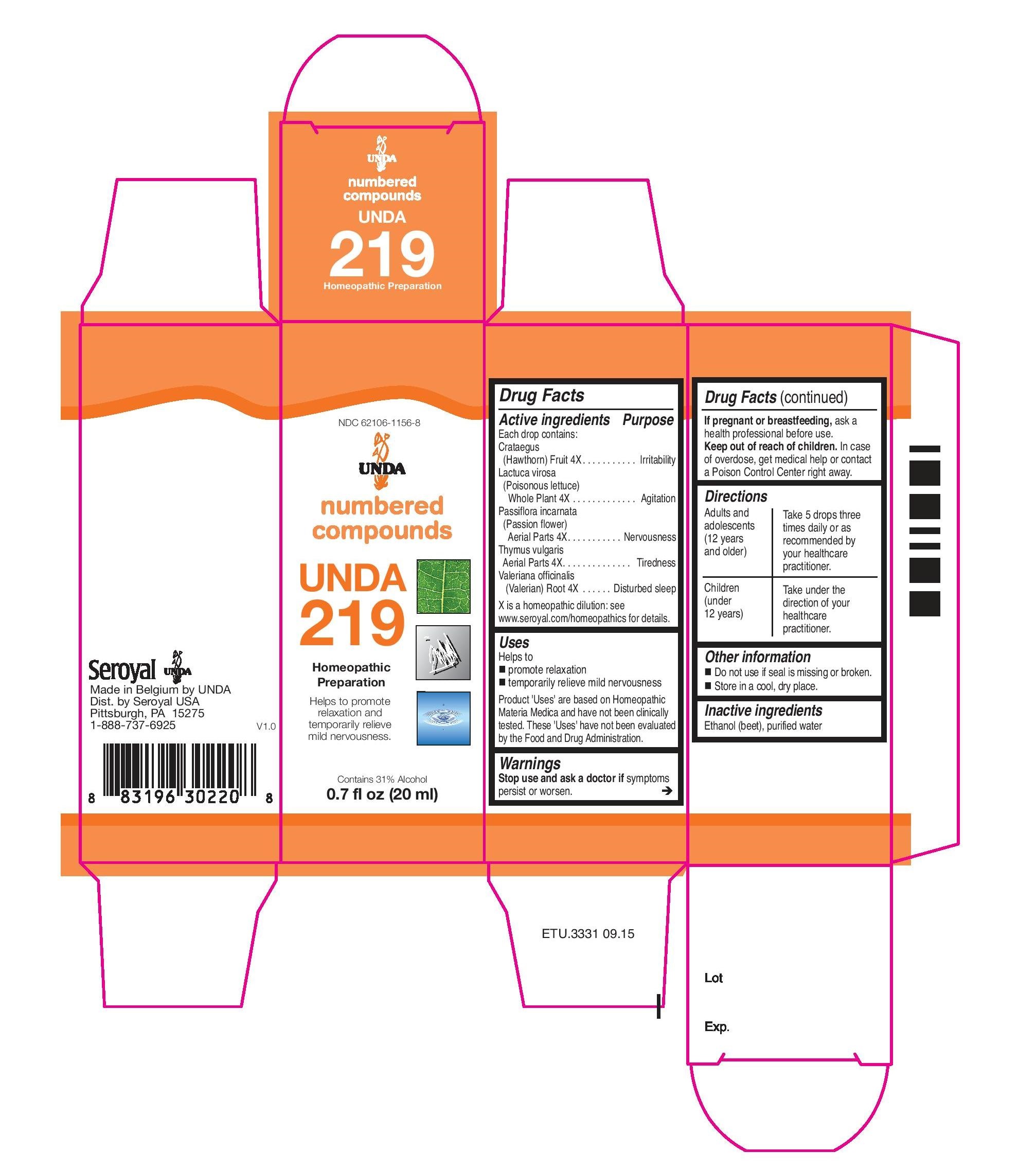 DRUG LABEL: UNDA 219
NDC: 62106-1156 | Form: LIQUID
Manufacturer: Seroyal USA
Category: homeopathic | Type: HUMAN OTC DRUG LABEL
Date: 20221109

ACTIVE INGREDIENTS: LACTUCA VIROSA 4 [hp_X]/20 mL; CRATAEGUS FRUIT 4 [hp_X]/20 mL; THYME 4 [hp_X]/20 mL; PASSIFLORA INCARNATA FLOWERING TOP 4 [hp_X]/20 mL; VALERIAN 4 [hp_X]/20 mL
INACTIVE INGREDIENTS: ALCOHOL; WATER

Unda 219

Active ingredients

Each drop contains:
Crataegus (Hawthorn) Fruit 4X
Lactuca virosa (Poisonous lettuce) Whole Plant 4X
Passiflora incarnata (Passion flower) Aerial Parts 4X
Thymus vulgaris Aerial Parts 4X
Valeriana officinalis (Valerian) Root 4X

Uses
Helps to promote relaxation and temporarily relieve mild nervousness

Warnings
Stop use and ask a doctor if symptoms persist or worsen.

If pregnant or breastfeeding, ask a health professional before use.
Keep out of reach of children.

In case of overdose, get medical help or contact a Poison Control Center right away.

Keep out of reach of children.

PREGNANCY OR BREAST FEEDING

If pregnant or breastfeeding, ask a health professional before use.

Other information
Do not use if seal is missing or broken.
Store in a cool, dry place.

Inactive ingredients
Ethanol (beet), purified water

Directions
Adults and adolescents (12 years and older)

Take 5 drops three times daily or as recommended by your healthcare practitioner.

Children (under 12 years)

Take under the direction of your healthcare practitioner

Uses
Helps to promote relaxation and temporarily relieve mild nervousness

Directions
Adults and adolescents (12 years and older): Take 5 drops three times daily or as
recommended by your healthcare practitioner.
Children (under 12 years): Take under the direction of your
healthcare practitioner.

PACKAGE LABEL

NDC 62106-1156-8

UNDA

numbered compounds

UNDA 219

Homeopathic Preparation

Helps to promote relaxation and temporarily relieve mild nervousness.

Contains 31% Alcohol
0.7 fl oz (20 ml)